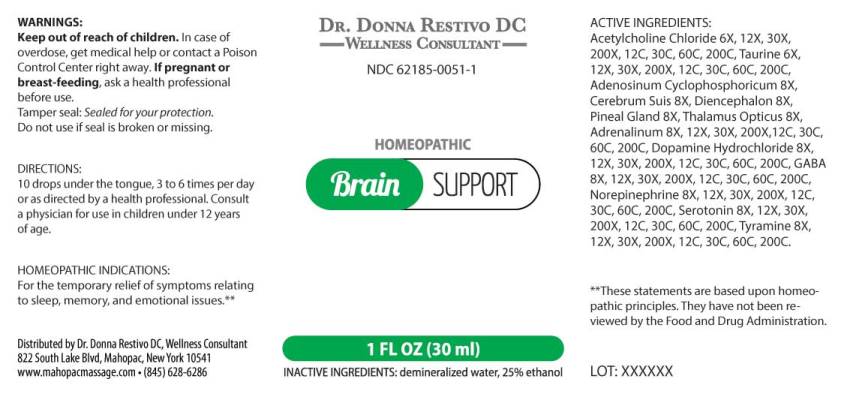 DRUG LABEL: Brain Support
NDC: 62185-0051 | Form: LIQUID
Manufacturer: Dr. Donna Restivo DC
Category: homeopathic | Type: HUMAN OTC DRUG LABEL
Date: 20240118

ACTIVE INGREDIENTS: ACETYLCHOLINE CHLORIDE 6 [hp_X]/1 mL; TAURINE 6 [hp_X]/1 mL; ADENOSINE CYCLIC PHOSPHATE 8 [hp_X]/1 mL; SUS SCROFA CEREBRUM 8 [hp_X]/1 mL; SUS SCROFA DIENCEPHALON 8 [hp_X]/1 mL; SUS SCROFA PINEAL GLAND 8 [hp_X]/1 mL; SUS SCROFA THALAMUS LATERAL GENICULATE NUCLEUS 8 [hp_X]/1 mL; EPINEPHRINE 8 [hp_X]/1 mL; DOPAMINE HYDROCHLORIDE 8 [hp_X]/1 mL; .GAMMA.-AMINOBUTYRIC ACID 8 [hp_X]/1 mL; NOREPINEPHRINE BITARTRATE 8 [hp_X]/1 mL; SEROTONIN HYDROCHLORIDE 8 [hp_X]/1 mL; TYRAMINE 8 [hp_X]/1 mL
INACTIVE INGREDIENTS: WATER; ALCOHOL

DRUG FACTS:

ACTIVE INGREDIENTS:

Acetylcholine Chloride 6X, 12X, 30X, 200X, 12C, 30C, 60C, 200C, Taurine 6X, 12X, 30X, 200X, 12C, 30C, 60C, 200C, Adenosinum Cyclophosphoricum 8X, Cerebrum (Suis) 8X, Diencephalon (Suis) 8X, Pineal Gland (Suis) 8X, Thalamus Opticus (Suis) 8X, Adrenalinum 8X, 12X, 30X, 200X, 12C, 30C, 60C, 200C, Dopamine Hydrochloride 8X, 12X, 30X, 200X, 12C, 30C, 60C, 200C, GABA (Gamma-Aminobutyric Acid) 8X, 12X, 30X, 200X, 12C, 30C, 60C, 200C, Norepinephrine (Bitartrate) 8X, 12X, 30X, 200X, 12C, 30C, 60C, 200C, Serotonin (Hydrochloride) 8X, 12X, 30X, 200X, 12C, 30C, 60C, 200C, Tyramine 8X, 12X, 30X, 200X, 12C, 30C, 60C, 200C.

HOMEOPATHIC INDICATIONS:

For the temporary relief of symptoms relating to sleep, memory, and emotional issues.**

**These statements are based upon homeopathic principles. They have not been reviewed by the Food and Drug Administration.

WARNINGS:

Keep out of reach of children. In case of overdose, get medical help or contact a Poison Control Center right away.

If pregnant or breast-feeding, ask a health professional before use.

Tamper seal: Sealed for your protection.

Do not use if seal is broken or missing.

Keep out of reach of children. In case of overdose, get medical help or contact a Poison Control Center right away.

DIRECTIONS:

10 drops under the tongue, 3 to 6 times per day or as directed by a health professional. Consult a physician for use in children under 12 years of age.

HOMEOPATHIC INDICATIONS:

For the temporary relief of symptoms relating to sleep, memory, and emotional issues.**

**These statements are based upon homeopathic principles. They have not been reviewed by the Food and Drug Administration.

INACTIVE INGREDIENTS:

demineralized water, 25% ethanol

QUESTIONS:

Distributed by Dr. Donna Restivo DC, Wellness Consultant

822 South Lake Blvd, Mahopac, New York 10541

www.mahopacmassage.com • (845) 628-6286

PACKAGE LABEL DISPLAY:

DR. DONNA RESTIVO DC
WELLNESS CONSULTANT
NDC 62185-0051-1
HOMEOPATHIC
Brain SUPPORT
1 FL OZ (30 ml)